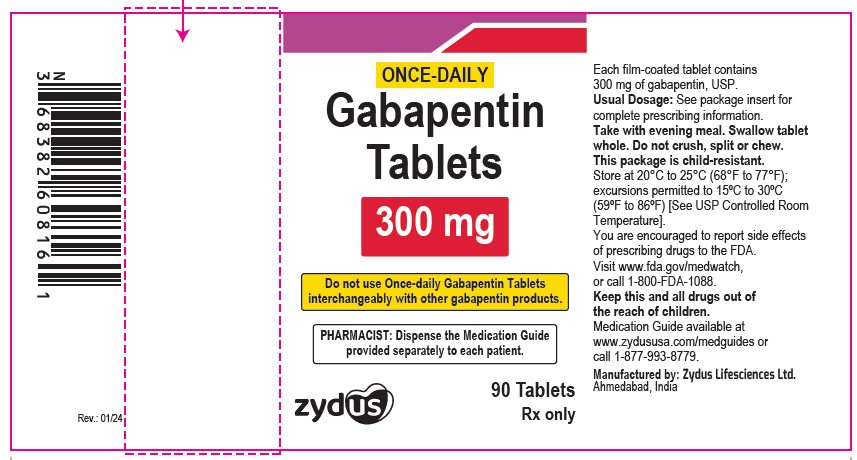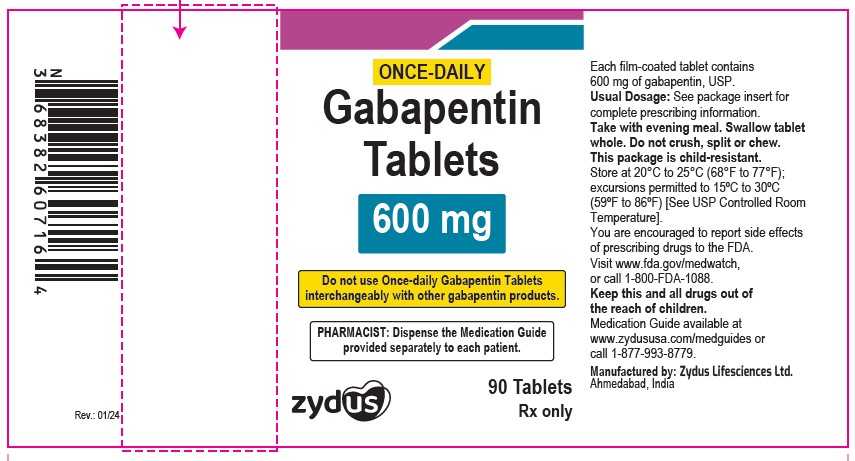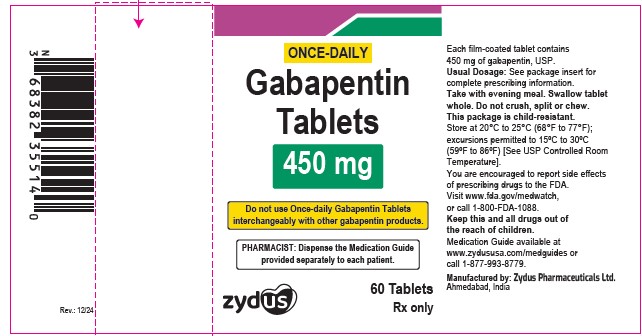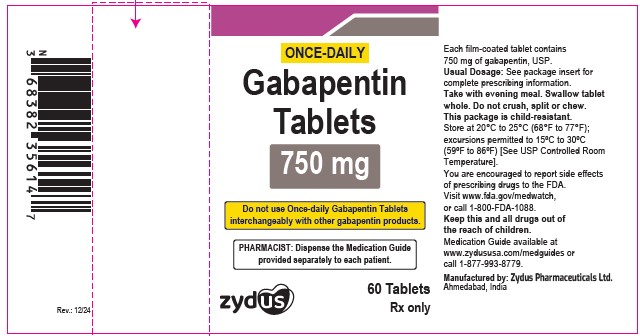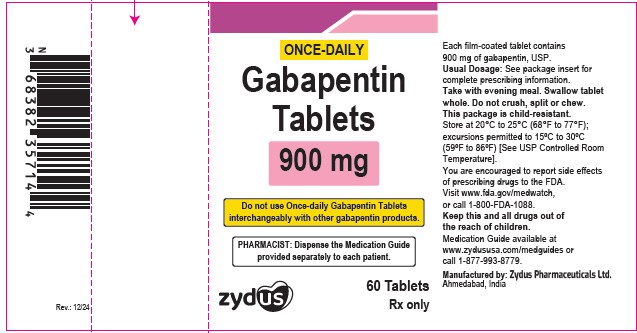 DRUG LABEL: gabapentin
NDC: 70771-1861 | Form: TABLET
Manufacturer: Zydus Lifesciences Limited
Category: prescription | Type: HUMAN PRESCRIPTION DRUG LABEL
Date: 20250915

ACTIVE INGREDIENTS: GABAPENTIN 300 mg/1 1
INACTIVE INGREDIENTS: CELLULOSE, MICROCRYSTALLINE; COPOVIDONE K25-31; HYPROMELLOSE, UNSPECIFIED; MAGNESIUM STEARATE; POLYETHYLENE GLYCOL, UNSPECIFIED; POVIDONE, UNSPECIFIED; TALC; TITANIUM DIOXIDE

Gabapentin Tablets

PACKAGE LABEL.PRINCIPAL DISPLAY PANEL

NDC 70771-1861-9 in bottle of 90 tablets

Gabapentin tablets, 300 mg

Rx only

90 tablets

gabapentin 300 mg

NDC 70771-1862-9 in bottle of 90 tablets

Gabapentin tablets, 600 mg

Rx only

90 tablets

gabapentin 600 mg

NDC 70771-1916-6 in bottle of 60 tablets

Gabapentin tablets, 450 mg

Rx only

60 tablets

NDC 70771-1917-6 in bottle of 60 tablets

Gabapentin tablets, 750 mg

Rx only

60 tablets

NDC 70771-1918-6 in bottle of 60 tablets

Gabapentin tablets, 900 mg

Rx only

60 tablets